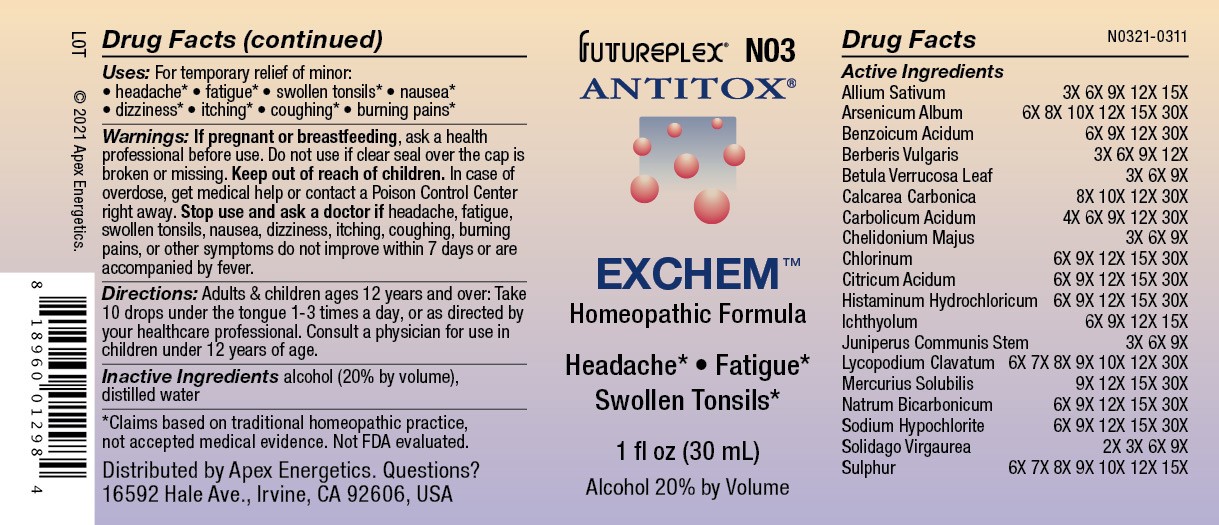 DRUG LABEL: N03
NDC: 63479-1403 | Form: SOLUTION/ DROPS
Manufacturer: Apex Energetics Inc.
Category: homeopathic | Type: HUMAN OTC DRUG LABEL
Date: 20240108

ACTIVE INGREDIENTS: JUNIPERUS COMMUNIS STEM 9 [hp_X]/1 mL; SODIUM HYPOCHLORITE 30 [hp_X]/1 mL; ARSENIC TRIOXIDE 30 [hp_X]/1 mL; PHENOL 30 [hp_X]/1 mL; CHELIDONIUM MAJUS 9 [hp_X]/1 mL; HISTAMINE DIHYDROCHLORIDE 30 [hp_X]/1 mL; ICHTHAMMOL 15 [hp_X]/1 mL; GARLIC 15 [hp_X]/1 mL; LYCOPODIUM CLAVATUM SPORE 30 [hp_X]/1 mL; MERCURIUS SOLUBILIS 30 [hp_X]/1 mL; SODIUM BICARBONATE 30 [hp_X]/1 mL; SOLIDAGO VIRGAUREA FLOWERING TOP 9 [hp_X]/1 mL; ANHYDROUS CITRIC ACID 30 [hp_X]/1 mL; BENZOIC ACID 30 [hp_X]/1 mL; BERBERIS VULGARIS ROOT BARK 12 [hp_X]/1 mL; BETULA PENDULA LEAF 9 [hp_X]/1 mL; OYSTER SHELL CALCIUM CARBONATE, CRUDE 30 [hp_X]/1 mL; CHLORINE 30 [hp_X]/1 mL; SULFUR 15 [hp_X]/1 mL
INACTIVE INGREDIENTS: WATER; ALCOHOL

N03

Active Ingredients
Allium Sativum | 3X 6X 9X 12X 15X
Arsenicum Album | 6X 8X 10X 12X 15X 30X
Benzoicum Acidum | 6X 9X 12X 30X
Berberis Vulgaris | 3X 6X 9X 12X
Betula Verrucosa Leaf | 3X 6X 9X
Calcarea Carbonica | 8X 10X 12X 30X
Carbolicum Acidum | 4X 6X 9X 12X 30X
Chelidonium Majus | 3X 6X 9X
Chlorinum | 6X 9X 12X 15X 30X
Citricum Acidum | 6X 9X 12X 15X 30X
Histaminum Hydrochloricum | 6X 9X 12X 15X 30X
Ichthyolum | 6X 9X 12X 15X
Juniperus Communis Stem | 3X 6X 9X
Lycopodium Clavatum | 6X 7X 8X 9X 10X 12X 30X
Mercurius Solubilis | 9X 12X 15X 30X
Natrum Bicarbonicum | 6X 9X 12X 15X 30X
Sodium Hypochlorite | 6X 9X 12X 15X 30X
Solidago Virgaurea | 2X 3X 6X 9X
Sulphur | 6X 7X 8X 9X 10X 12X 15X

Uses:

PURPOSE

For temporary relief of minor:

headache*

fatigue*

swollen tonsils*

nausea*

dizziness*

itching*

coughing*

burning pains*

*Claims based on traditional homeopathic practice, not accepted medical evidence. Not FDA evaluated.

Warnings:

PREGNANCY OR BREAST FEEDING

If pregnant or breastfeeding, ask a health professional before use.

Do not use if clear seal over the cap is broken or missing.

Keep out of reach of children. In case of overdose, get medical help or contact a Poison Control Center right away.

Stop use and ask a doctor if headache, fatigue, swollen tonsils, nausea, dizziness, itching, coughing, burning pains, or other symptoms do not improve within 7 days or are accompanied by fever.

DOSAGE AND ADMINISTRATION

Adults & children ages 12 years and over: Take 10 drops under the tongue 1-3 times a day, or as directed by your healthcare professional. Consult a physician for use in children under 12 years of age.

INACTIVE INGREDIENT

alcohol (20% by volume), distilled water

Distributed by Apex Energetics. Questions?

16592 Hale Ave., Irvine, CA 92606, USA

PACKAGE LABEL

FUTUREPLEX® N03

ANTITOX®

EXCHEM™

Homeopathic Formula

Headache* Fatigue*

Swollen Tonsils*

1 fl oz (30 mL)

Alcohol 20% by Volume